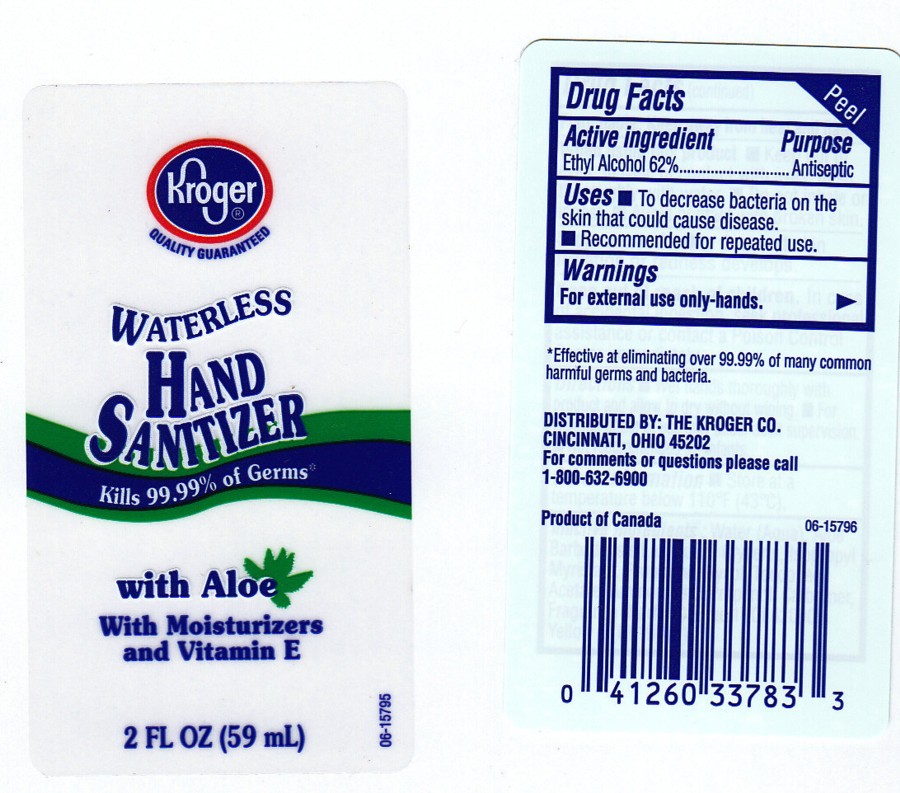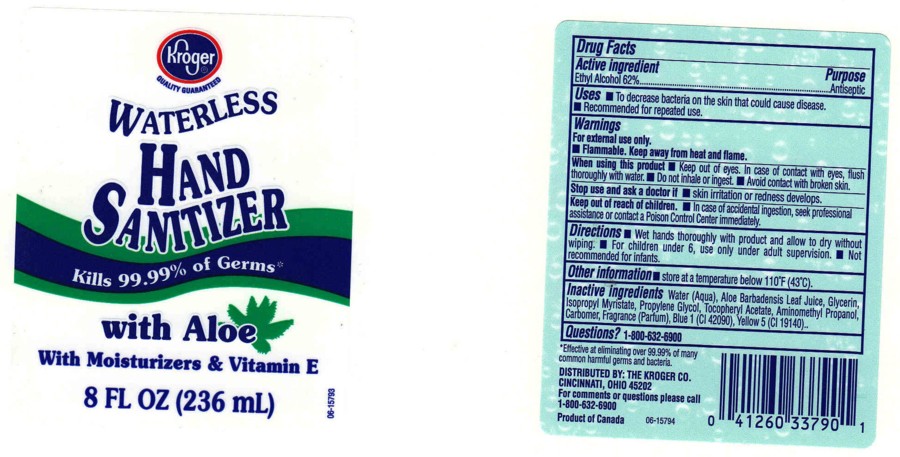 DRUG LABEL: INSTANT HAND SANITIZER
NDC: 59450-223 | Form: GEL
Manufacturer: THE KROGER CO
Category: otc | Type: HUMAN OTC DRUG LABEL
Date: 20100220

ACTIVE INGREDIENTS: ALCOHOL 62.0000 mL/100 mL
INACTIVE INGREDIENTS: FD&C YELLOW NO. 5 0.0001 mL/100 mL

HAND SANITIZER WITH ALOE

ACTIVE INGREDIENT

ETHYL ALCOHOL 62% (ANTISEPTIC)

USES

TO HELP REDUCE BACTERIA ON THE SKIN

WARNINGS

- FOR EXTERNAL USE ONLY.
- FLAMMABLE. KEEP AWAY FROM FIRE OR FLAME.

WHEN USING THIS PRODUCT

AVOID CONTACT WITH EYES. IF CONTACT OCCURS, RINSE WITH WATER.

STOP USE AND ASK A DOCTOR IF

SKIN IRRITATION OR REDNESS DEVELOPS.

KEEP OUT OF REACH OF CHILDREN

IN CASE OF ACCIDENTAL INGESTION, GET MEDICAL HELP OR CONTACT A POISON CONTROL CENTER IMMEDIATELY.

OTHER INFORMATION

STORE AT A TEMPERATURE BELOW 110^0F (43^0C).

PACKAGE FRONT AND BACK LABELS

- kroger2.jpg
- kroger8.jpg